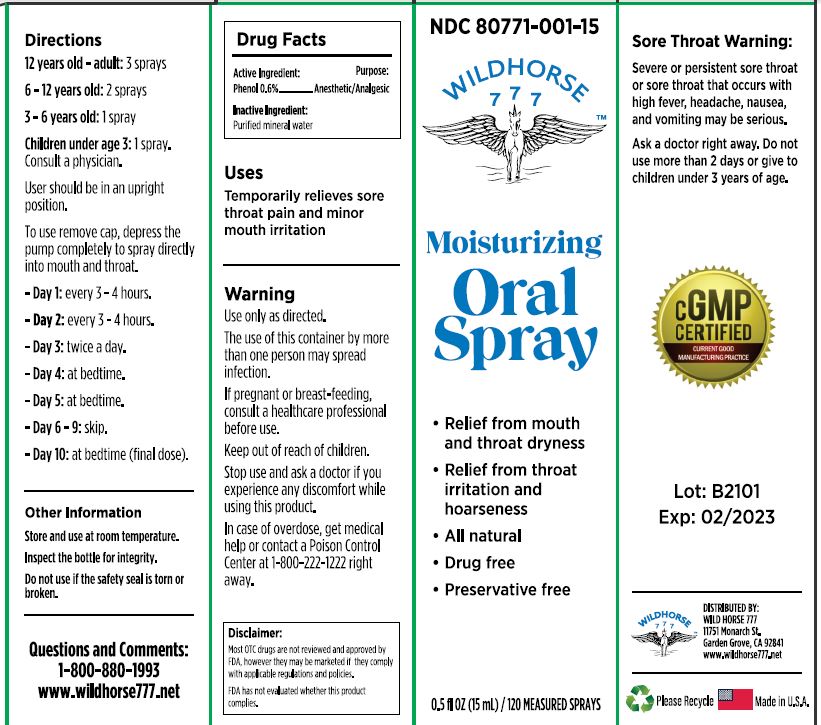 DRUG LABEL: Wild Horse 777 Oral
NDC: 80771-001 | Form: LIQUID
Manufacturer: Wild Horse 777, Inc.
Category: otc | Type: HUMAN OTC DRUG LABEL
Date: 20231110

ACTIVE INGREDIENTS: PHENOL 6 mg/1 mL
INACTIVE INGREDIENTS: WATER

Wild Horse 777 Oral Spray

Active Ingredient:

Phenol 0.6%

Purpose:

Anesthetic/Analgesic

Uses

Temporarily relieves sore throate pain and minor mouth irritation.

Warnings

- Use only as directed.

- The use of this container by more than one person may spread infection.

If pregnant or breastfeeding,

consult a health care professional before use.

Stop use and ask a doctor

- if you experience any discomfort while using this product.

- In case of overdose, get medical help or contact a Poison Control Center at 1-800-222-1222 right away.

Directions

- 12 years old - adult:3 sprays.

- 6-12 years old: 2 sprays.

- 3-6 years old: 1 spray.

- Children under age 3:1 spray. Consult a physician.

- User should be in an upright position.

- To use, remove cap, depress the pump completely to spray directly into mouth and throat.

- Each spray is followed by a small sip of lukewarm water (<100 °F).

- Swish water thoroughly for a few seconds, then swallow.

- Day 1: every 3-4 hours.

- Day 2: every 3-4 hours.

- Day 3: twice a day.

- Day 4: at bedtime.

- Day 5: at bedtime.

- Day 6-9: skip.

- Day 10: at bedtime (final dose).

Other Information

- Store and use at room temperature.

- Inspect the bottle for integrity.

- Do not use if the safety seal is torn or broken.

Inactive Ingredient:

Purified mineral water

Questions and Comments:

1-800-880-1993 www.wildhorse777.net